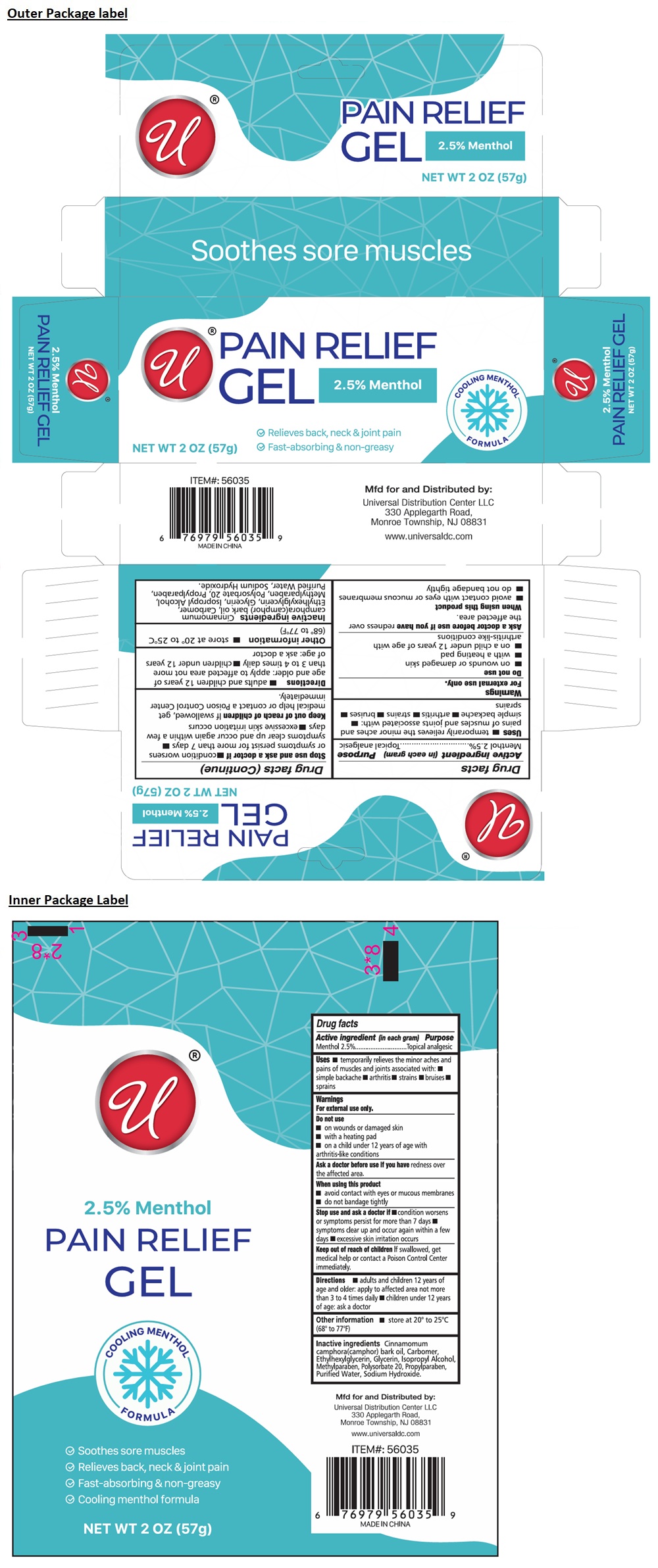 DRUG LABEL: 2.5% Menthol PAIN RELIEF
NDC: 43473-096 | Form: GEL
Manufacturer: Nantong Health & Beyond Hygienic Products Inc.
Category: otc | Type: HUMAN OTC DRUG LABEL
Date: 20260205

ACTIVE INGREDIENTS: MENTHOL, UNSPECIFIED FORM 25 mg/1 g
INACTIVE INGREDIENTS: CAMPHOR OIL; CARBOMER HOMOPOLYMER, UNSPECIFIED TYPE; ETHYLHEXYLGLYCERIN; GLYCERIN; ISOPROPYL ALCOHOL; METHYLPARABEN; POLYSORBATE 20; PROPYLPARABEN; WATER; SODIUM HYDROXIDE

43473-096 2.5% Menthol PAIN RELIEF GEL

Active ingredient (in each gram)

Menthol 2.5%

Purpose

Topical analgesic

Uses

• temporarily relieves the minor aches and pains of muscles and joints associated with: • simple backache • arthritis • strains • bruises • sprains

Warnings

For external use only.

Do not use
• on wounds or damaged skin
• with a heating pad
• on a child under 12 years of age with arthritis-like conditions

Ask a doctor before use if you have redness over the affected area.

When using this product
• avoid contact with eyes or mucous membranes
• do not bandage tightly

Stop use and ask a doctor if • condition worsens or symptoms persist for more than 7 days • symptoms clear up and occur again within a few days • excessive skin irritation occurs

KEEP OUT OF REACH OF CHILDREN

Keep out of reach of childrenIf swallowed, get medical help or contact a Poison Control Center immediately.

Directions

• adults and children 12 years of age and older: apply to affected area not more than 3 to 4 times daily • children under 12 years of age: ask a doctor

Other information

• store at 20° to 25°C (68° to 77°F)

Inactive ingredients

Cinnamomum camphora(camphor) bark oil, Carbomer, Ethylhexylglycerin, Glycerin, Isopropyl Alcohol, Methylparaben, Polysorbate 20, Propylparaben, Purified Water, Sodium Hydroxide.

COOLING MENTHOL FORMULA

✓ Relives back, neck & joint pain

✓ Fast-absorbing & non-greasy

Soothes sore muscles

Mfd for and Distributed by:
Universal Distribution Center LLC
330 Applegarth Road,
Monroe Township, NJ 08831

www.universaldc.com

MADE IN CHINA